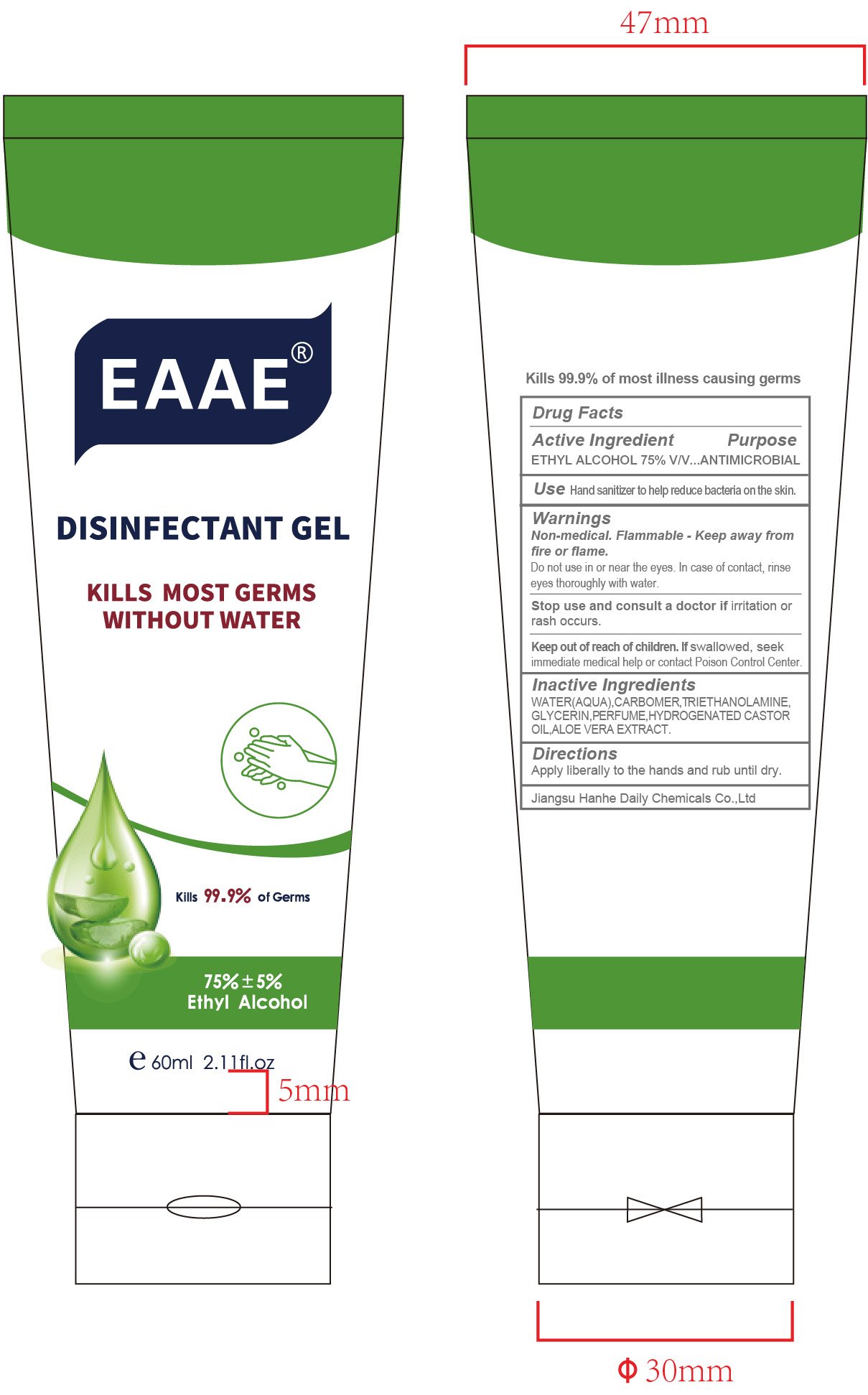 DRUG LABEL: EAAE Disinfectant
NDC: 73027-204 | Form: GEL
Manufacturer: JIANGSU HANHE DAILY CHEMICALS CO., LTD.
Category: otc | Type: HUMAN OTC DRUG LABEL
Date: 20211102

ACTIVE INGREDIENTS: ALCOHOL 75 mL/100 mL
INACTIVE INGREDIENTS: CARBOMER 934; TROLAMINE; GLYCERIN; HYDROGENATED CASTOR OIL; ALOE VERA WHOLE

ACTIVE INGREDIENT

Ethyl Alcohol 75% v/v

Purpose

Antimicrobial

Use

Hand sanitizer to help reduce bacteria on the skin

Warnings

For external use only.

Non Medical. Flammable. Keep away from fire or flame

When using this product, do not use in or near eyes, In case of contact, rinse eyes thoroughly with water

Stop use and consult a doctor if irritation or rash occurs

Keep out of reach of children. If swallowed, seek immmediate medical help or contact a poison control center

Directions

- Apply liberally to the hands and rub until dry

Inactive ingredients

Water, Carbomer, Triethanolamine, Glycerin, Perfume, Castor Oil, Hydrogenated, Aloe Vera Extract